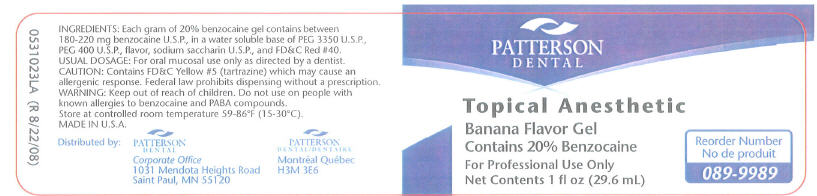 DRUG LABEL: Topical Anesthetic 
NDC: 50227-2116 | Form: GEL, DENTIFRICE
Manufacturer: Patterson Dental
Category: prescription | Type: HUMAN PRESCRIPTION DRUG LABEL
Date: 20100513

ACTIVE INGREDIENTS: Benzocaine 220 mg/1 g
INACTIVE INGREDIENTS: POLYETHYLENE GLYCOL 3350; POLYETHYLENE GLYCOL 400; SACCHARIN SODIUM; FD&C RED NO. 40

Topical Anesthetic
Banana Flavor Gel

INGREDIENTS

Each gram of 20% benzocaine gel contains between 180-220 mg benzocaine U.S.P., in a water soluble base of PEG 3350 U.S.P., PEG 400 U.S.P., flavor, sodium saccharin U.S.P., and FD&C Red #40.

USUAL DOSAGE

For oral mucosal use only as directed by a dentist.

CAUTION

Contains FD&C Yellow #5 (tartrazine) which may cause an allergenic response. Federal law prohibits dispensing without a prescription.

WARNING

Keep out of reach of children. Do not use on people with known allergies to benzocaine and PABA compounds.

HOW SUPPLIED

STORAGE AND HANDLING

Store at controlled room temperature 59-86°F (15-30°C).

MADE IN U.S.A.

Distributed by:

PATTERSON
DENTAL
Corporate Office
1031 Mendota Heights Road
Saint Paul, MN 55120

PATTERSON
DENTAL /
Montréal Québec
H3M 3E6

PRINCIPAL DISPLAY PANEL - 29.6 mL Label

PATTERSON
DENTAL

Topical Anesthetic

Banana Flavor Gel
Contains 20% Benzocaine

For Professional Use Only
Net Contents 1 fl oz (29.6 mL)

Reorder Number
089-9989